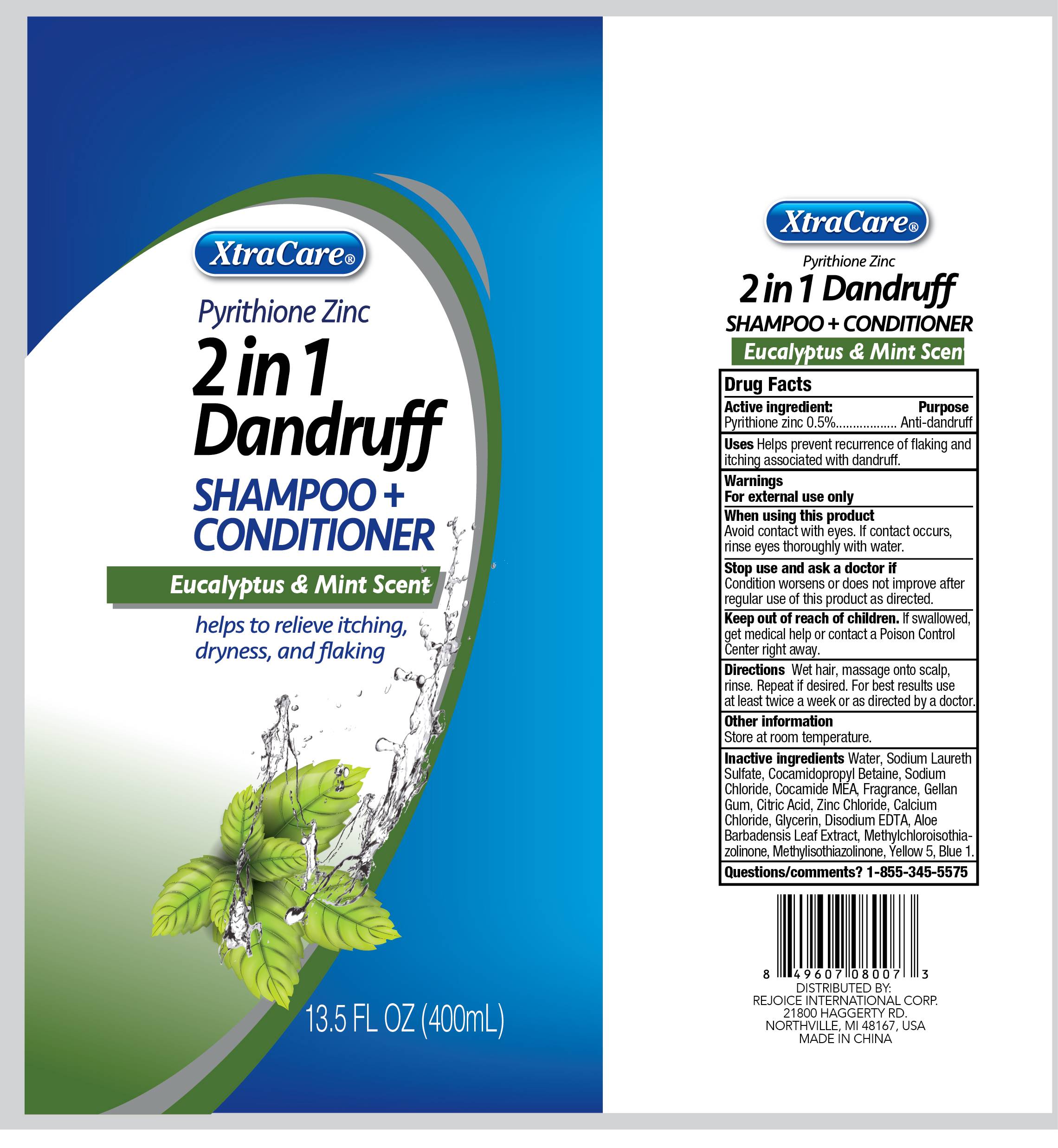 DRUG LABEL: 13.5oz 2 In 1 Dandruff Hair Cleanse and Conditioner - Eucalyptus and Mint
NDC: 58503-210 | Form: SHAMPOO
Manufacturer: China Ningbo Shangge Cosmetics Technology Corp.
Category: otc | Type: HUMAN OTC DRUG LABEL
Date: 20250421

ACTIVE INGREDIENTS: PYRITHIONE ZINC 0.5 g/100 mL
INACTIVE INGREDIENTS: COCAMIDE MEA; GLYCERIN; COCAMIDOPROPYL BETAINE; CALCIUM CHLORIDE; WATER; EDETATE DISODIUM; SODIUM LAURETH SULFATE; METHYLISOTHIAZOLINONE; CITRIC ACID; ZINC CHLORIDE; BLUE 1; ALOE BARBADENSIS LEAF; YELLOW 5; GELLAN GUM; SODIUM CHLORIDE; METHYLCHLOROISOTHIAZOLINONE

Active ingredient

Pyrithione Zinc 0.5%

Purpose

Anti-dandruff

Use

Helps prevent recurrence of flaking and itching associsted with dandruff.

Warnings

For external use only

When using this product

Avoid contact with eyes. If contact occurs, rinse eyes thoroughly with water.

Stop use and ask a doctor if

Condition worsens or does not improve after regular use of this products as directed.

Keep out of reach of children

If swallowed, get medical help or contact a Poison Control Center right away.

Directions

Wet hair, massage onto scalp, rinse. Repeat if desired. For best resultd use at least twice a week or as directed by a doctor

Other information

Store at room temperature.

Inactive ingredients

Water
Sodium Laureth Sulfate
Cocamidopropyl Betaine
Sodium Chloride
Cocamide MEA
Fragrance
Gellan Gum
Citric Acid
Zinc Chloride
Calcium Chloride
Glycerin
Disodium EDTA
Aloe Barbadensis Leaf Extract
Methylchloroisothiazolinone
Methylisothiazolinone
Yellow 5
Blue 1